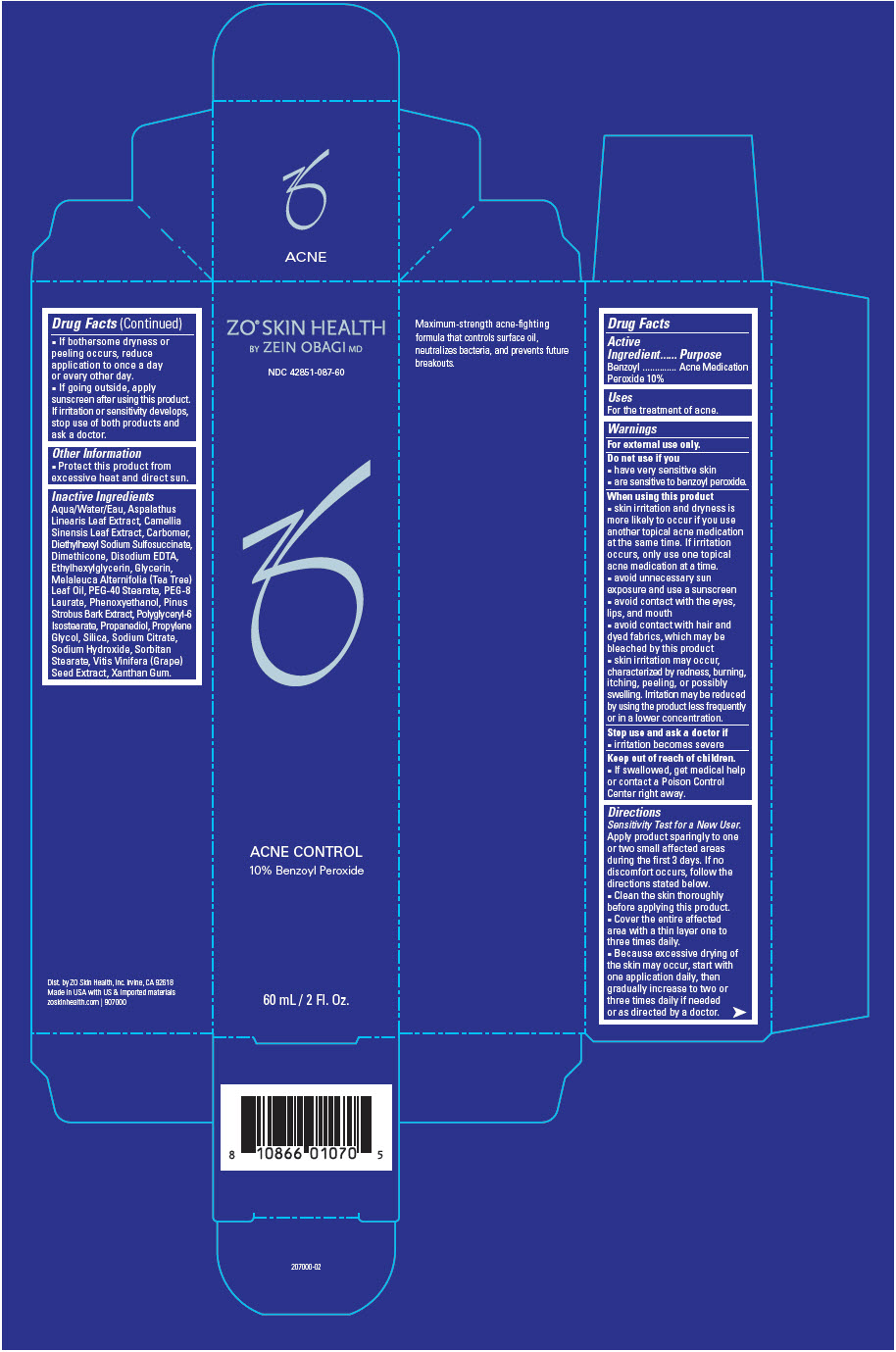 DRUG LABEL: ZO Skin Health Acne Control Benzoyl Peroxide
NDC: 42851-087 | Form: CREAM
Manufacturer: ZO Skin Health, Inc.
Category: otc | Type: HUMAN OTC DRUG LABEL
Date: 20241028

ACTIVE INGREDIENTS: BENZOYL PEROXIDE 100 mg/1 mL
INACTIVE INGREDIENTS: WATER; ASPALATHUS LINEARIS LEAF; GREEN TEA LEAF; CARBOMER HOMOPOLYMER, UNSPECIFIED TYPE; DOCUSATE SODIUM; DIMETHICONE; EDETATE DISODIUM ANHYDROUS; ETHYLHEXYLGLYCERIN; GLYCERIN; TEA TREE OIL; PEG-40 STEARATE; PEG-8 LAURATE; PHENOXYETHANOL; PINUS STROBUS BARK; POLYGLYCERYL-6 ISOSTEARATE; PROPANEDIOL; PROPYLENE GLYCOL; SILICON DIOXIDE; SODIUM CITRATE, UNSPECIFIED FORM; SODIUM HYDROXIDE; SORBITAN MONOSTEARATE; VITIS VINIFERA SEED; XANTHAN GUM

ZO® Skin Health Acne Control 10% Benzoyl Peroxide
National Drug Code 42851-087-60

Drug Facts

Active Ingredient

Benzoyl Peroxide 10%

Purpose

Acne Medication

Uses

For the treatment of acne.

Warnings

For external use only.

Do not use if you

- have very sensitive skin
- are sensitive to benzoyl peroxide.

When using this product

- skin irritation and dryness is more likely to occur if you use another topical acne medication at the same time. If irritation occurs, only use one topical acne medication at a time.
- avoid unnecessary sun exposure and use a sunscreen
- avoid contact with the eyes, lips, and mouth
- avoid contact with hair and dyed fabrics, which may be bleached by this product
- skin irritation may occur, characterized by redness, burning, itching, peeling, or possibly swelling. Irritation may be reduced by using the product less frequently or in a lower concentration.

Stop use and ask a doctor if

- irritation becomes severe

Keep out of reach of children.

- If swallowed, get medical help or contact a Poison Control Center right away.

Directions

Sensitivity Test for a New User.

Apply product sparingly to one or two small affected areas during the first 3 days. If no discomfort occurs, follow the directions stated below.

- Clean the skin thoroughly before applying this product.
- Cover the entire affected area with a thin layer one to three times daily.
- Because excessive drying of the skin may occur, start with one application daily, then gradually increase to two or three times daily if needed or as directed by a doctor.
- If bothersome dryness or peeling occurs, reduce application to once a day or every other day.
- If going outside, apply sunscreen after using this product. If irritation or sensitivity develops, stop use of both products and ask a doctor.

Other Information

- Protect this product from excessive heat and direct sun.

Inactive Ingredients

Aqua/Water/Eau, Aspalathus Linearis Leaf Extract, Camellia Sinensis Leaf Extract, Carbomer, Diethylhexyl Sodium Sulfosuccinate, Dimethicone, Disodium EDTA, Ethylhexylglycerin, Glycerin, Melaleuca Alternifolia (Tea Tree) Leaf Oil, PEG-40 Stearate, PEG-8 Laurate, Phenoxyethanol, Pinus Strobus Bark Extract, Polyglyceryl-6 Isostearate, Propanediol, Propylene Glycol, Silica, Sodium Citrate, Sodium Hydroxide, Sorbitan Stearate, Vitis Vinifera (Grape) Seed Extract, Xanthan Gum.

Dist. by ZO Skin Health, Inc. Irvine, CA 92618

PRINCIPAL DISPLAY PANEL - 60 mL Tube Carton

ZO® SKIN HEALTH
BY ZEIN OBAGI MD

NDC 42851-087-60

ACNE CONTROL
10% Benzoyl Peroxide

60 mL / 2 Fl. Oz.